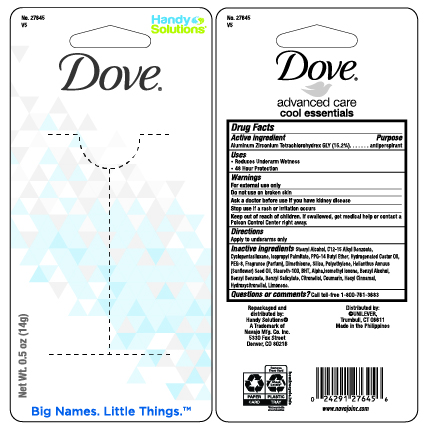 DRUG LABEL: HANDY SOLUTIONS DOVE COOL ESSENTIAL CUCUMBER AND GREEN TEA SCENT ANTI-PERSPIRANT
NDC: 67751-134 | Form: STICK
Manufacturer: Navajo Manufacturing Company Inc.
Category: otc | Type: HUMAN OTC DRUG LABEL
Date: 20241002

ACTIVE INGREDIENTS: ALUMINUM ZIRCONIUM TETRACHLOROHYDREX GLY 14.8 g/100 g
INACTIVE INGREDIENTS: CYCLOMETHICONE 5; PPG-14 BUTYL ETHER; STEARYL ALCOHOL; HYDROGENATED CASTOR OIL; BUTYLATED HYDROXYTOLUENE; STEARETH-100; SUNFLOWER OIL; ALKYL (C12-15) BENZOATE

Dove Ultimate Go Fresh Cool Essentials

Active Ingredient

Aluminum Zirconium Tetrachlorohydrex GLY (15.2%)

Purpose

anti-perspirant

Uses

- reduces underarm wetness
- 24 Hour Protection

Warnings

For External Use Only

Do not use

on broken skin

Ask a doctor before use if

you have kidney disease

Stop use

if rash or irritation occurs

Keep out of reach of children.

If swallowed, get medical help or contact a Poison Control Center right away.

Directions

- apply to underarms only

Other information

Do not store over 115oF (46oC)

Inactive ingredients:

Cyclopentasiloxane, Stearyl Alcohol, C12-15 Alkyl Benzoate, PPG-14 Butyl Ether, Hydrogenated Castor Oil, Fragrance (Parfum), Dimethicone, Polyethylene, Helianthus Annuus (Sunflower) Seed Oil, Steareth-100, BHT.

Questions or comments?

- 1-800-761-DOVE